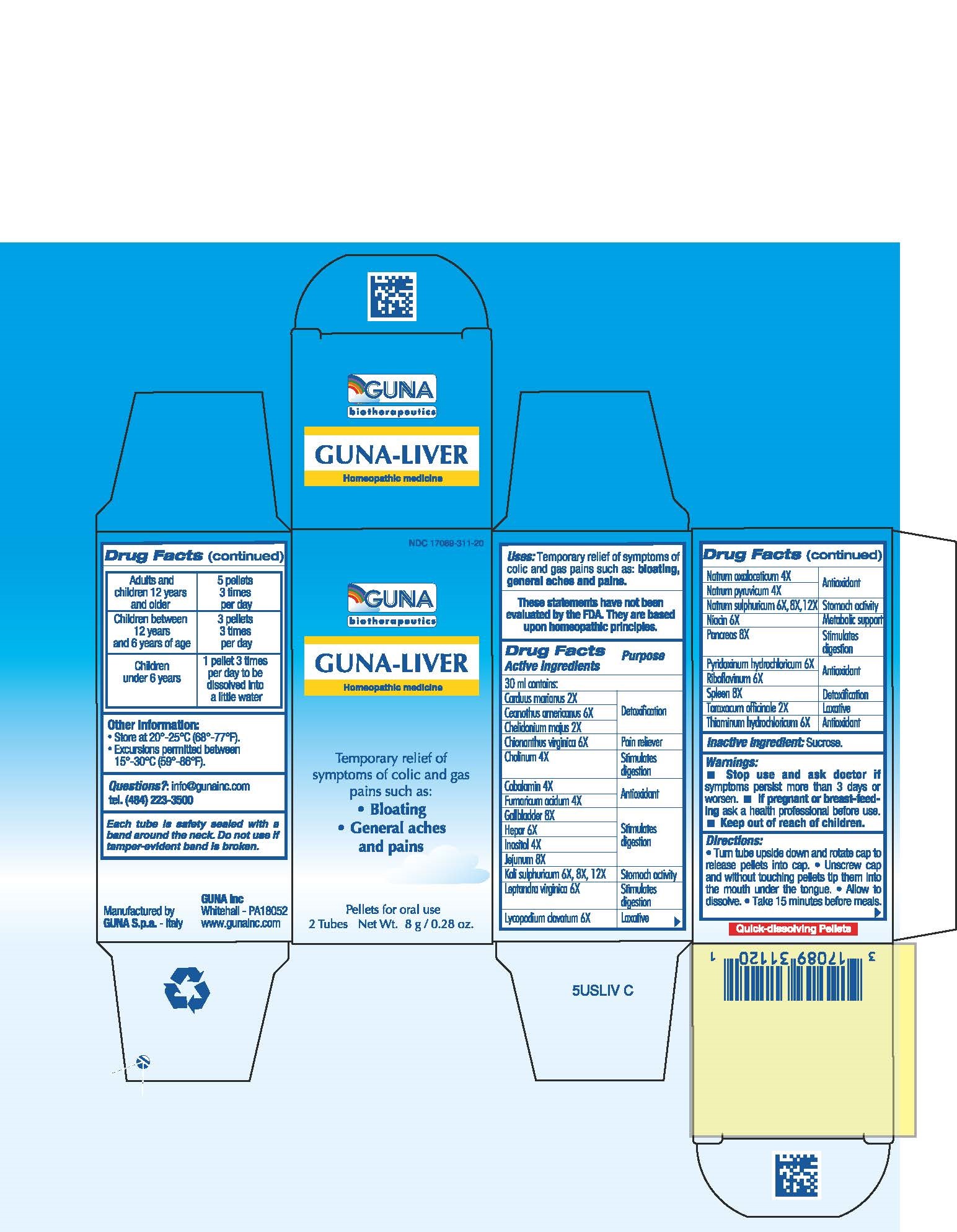 DRUG LABEL: GUNA-LIVER
NDC: 17089-311 | Form: PELLET
Manufacturer: Guna spa
Category: homeopathic | Type: HUMAN OTC DRUG LABEL
Date: 20181221

ACTIVE INGREDIENTS: SILYBUM MARIANUM SEED 2 [hp_X]/4 g; CEANOTHUS AMERICANUS LEAF 6 [hp_X]/4 g; CHELIDONIUM MAJUS 2 [hp_X]/4 g; CHIONANTHUS VIRGINICUS BARK 6 [hp_X]/4 g; CHOLINE HYDROXIDE 4 [hp_X]/4 g; COBALAMIN 4 [hp_X]/4 g; FUMARIC ACID 4 [hp_X]/4 g; SUS SCROFA GALLBLADDER 8 [hp_X]/4 g; PORK LIVER 6 [hp_X]/4 g; INOSITOL 4 [hp_X]/4 g; SUS SCROFA JEJUNUM 8 [hp_X]/4 g; POTASSIUM SULFATE 12 [hp_X]/4 g; CULVER'S ROOT 6 [hp_X]/4 g; LYCOPODIUM CLAVATUM SPORE 6 [hp_X]/4 g; SODIUM DIETHYL OXALACETATE 4 [hp_X]/4 g; SODIUM PYRUVATE 4 [hp_X]/4 g; SODIUM SULFATE 8 [hp_X]/4 g; NIACIN 6 [hp_X]/4 g; SUS SCROFA PANCREAS 8 [hp_X]/4 g; PYRIDOXINE HYDROCHLORIDE 6 [hp_X]/4 g; RIBOFLAVIN 6 [hp_X]/4 g; SUS SCROFA SPLEEN 8 [hp_X]/4 g; TARAXACUM OFFICINALE 2 [hp_X]/4 g; THIAMINE HYDROCHLORIDE 6 [hp_X]/4 g
INACTIVE INGREDIENTS: SUCROSE

GUNA-LIVER

ACTIVE INGREDIENT

Carduus marianus 2X DETOXIFICATION
Ceanothus americanus 6X DETOXIFICATION
Chelidonium majus 2X DETOXIFICATION
Chionanthus virginica 6X PAIN RELIEVER
Cholinum 4X STIMULATES DIGESTION
Cobalamin 4X ANTIOXIDANT
Fumaricum acidum 4X ANTIOXIDANT
Gall bladder 8X STIMULATES DIGESTION
Hepar 6X STIMULATES DIGESTION

Inositol 4X STIMULATES DIGESTION
Jejunum 8X STIMULATES DIGESTION
Kali sulphuricum 6X 8X 12X STOMACH ACTIVITY
Leptandra virginica 6X STIMULATES DIGESTION
Lycopodium clavatum 6X LAXATIVE
Natrum oxalaceticum 4X ANTIOXIDANT
Natrum pyruvicum 4X ANTIOXIDANT
Natrum sulphuricum 6X 8X 12X STOMACH ACTIVITY
Niacin 6X METABOLIC SUPPORT
Pancreas 8X STIMULATES DIGESTION
Pyridoxinum hydrochloricum 6X ANTIOXIDANT
Riboflavinum 6X ANTIOXIDANT
Spleen 8X DETOXIFICATION
Taraxacum officinale 2X LAXATIVE
Thiaminum hydrochloricum 6X ANTIOXIDANT

PURPOSE

Temporary relief of symptoms of colic and gas pains such as:

- Bloating
- General aches and pains

Stop use and ask doctor if symptoms persist more than 5 days or worsen.
If pregnant or breast-feeding ask a health professional before use.
Keep out of reach of children.

PREGNANCY OR BREAST FEEDING

If pregnant or breast-feeding ask a health professional before use.

Keep out of reach of children

DOSAGE AND ADMINISTRATION

Adults and children 12 years and older 5 pellets 3 times per day
Children between 12 years and 6 years of age 3 pellets 3 times per day
Children under 6 years 1 pellet 3 times per day to be dissolved into a little water

Questions?: info@gunainc.com
tel. (484) 223-3500

INDICATIONS AND USAGE

Turn tube upside down and rotate cap to release pellets into cap.
Unscrew cap and without touching pellets tip them into the mouth under the tongue.
Allow to dissolve
Take 15 minutes before meals.

Inactive ingredient: Sucrose.